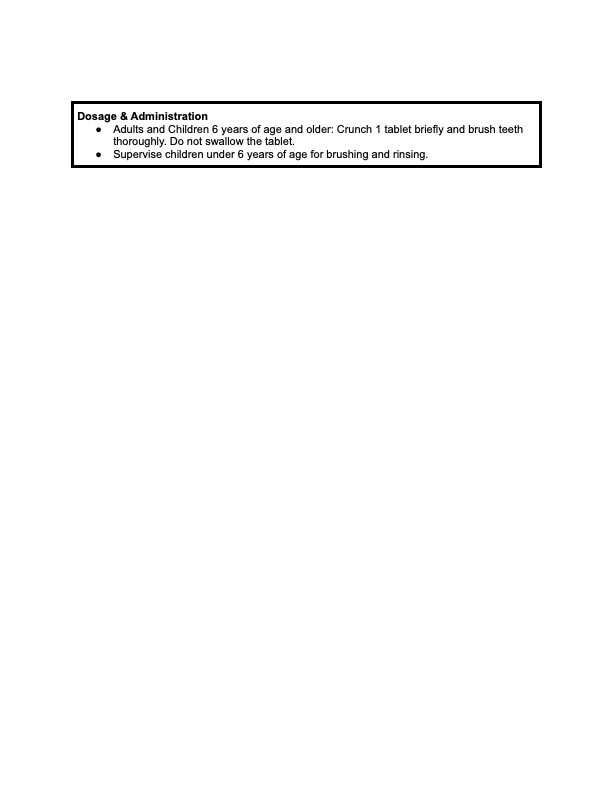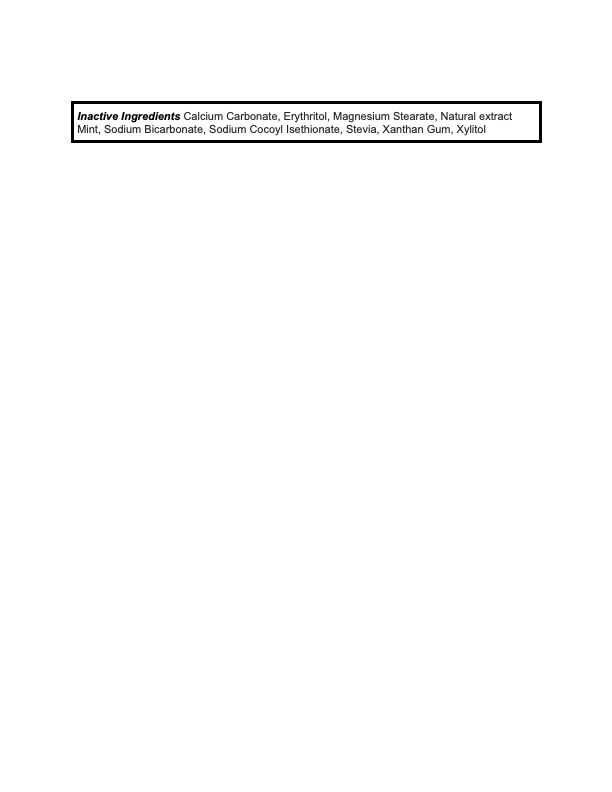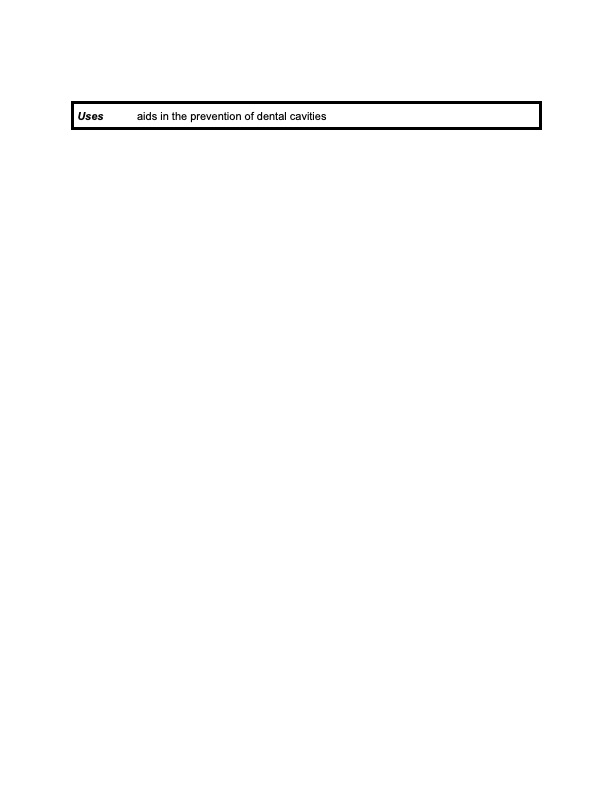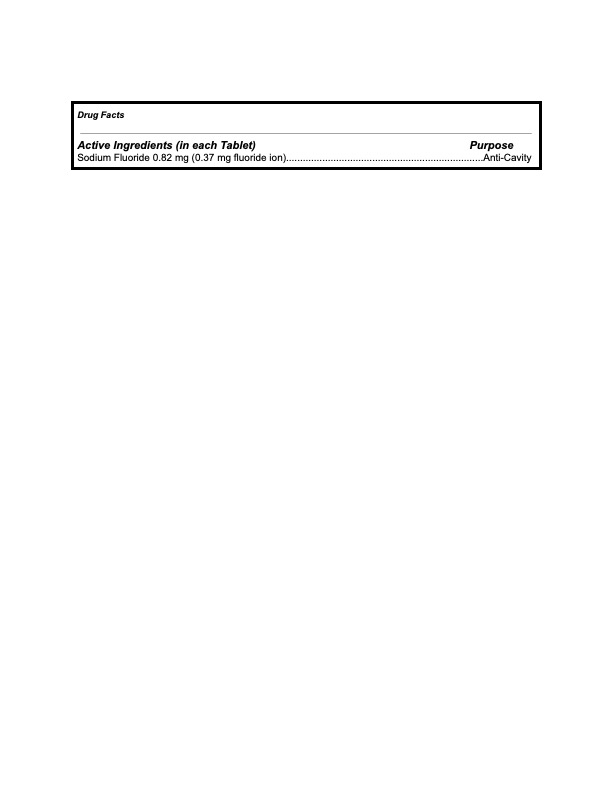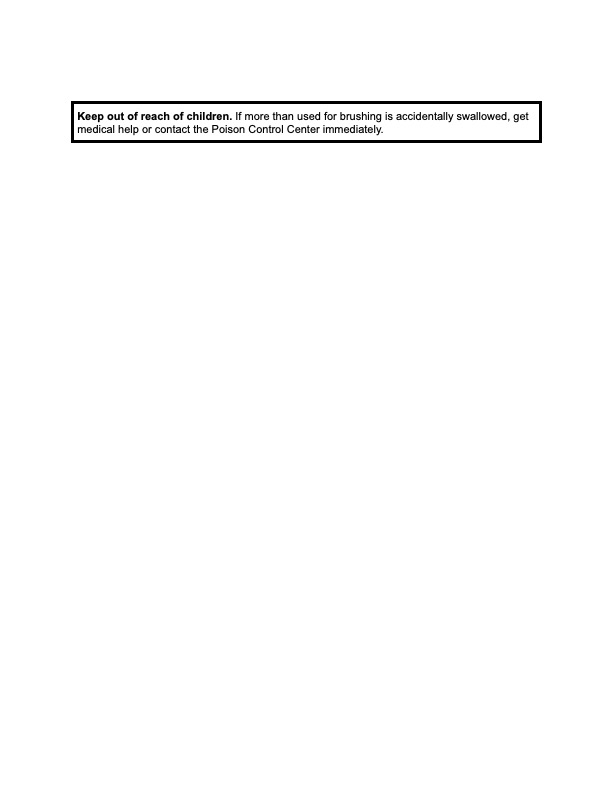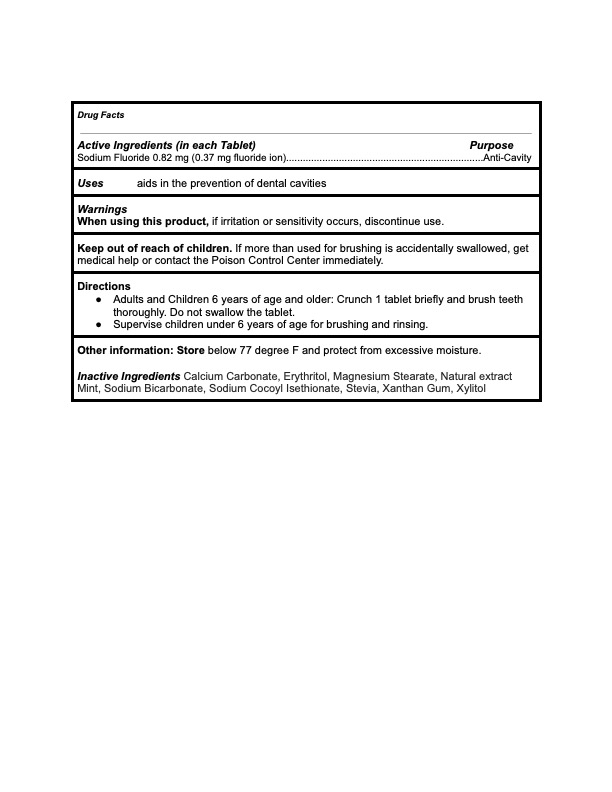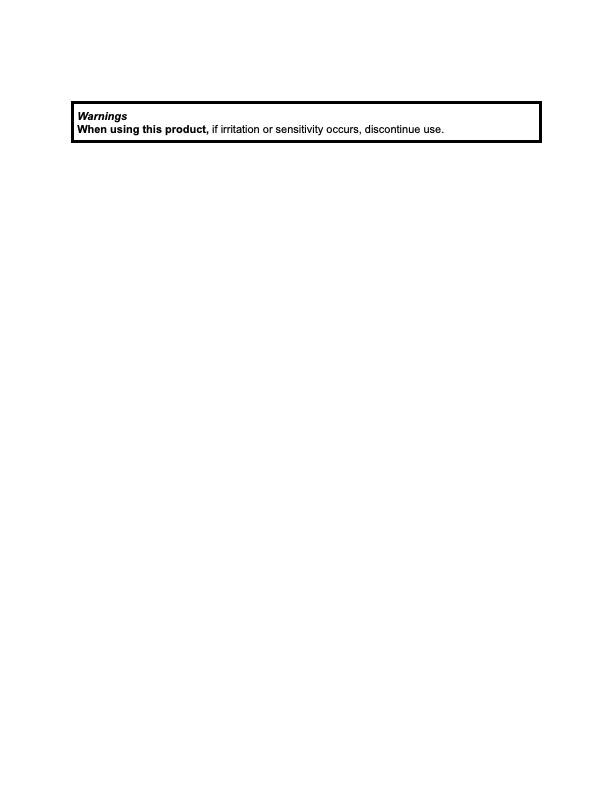 DRUG LABEL: KAYLAAN
NDC: 82091-113 | Form: TABLET, CHEWABLE
Manufacturer: Kaylaan LLC
Category: otc | Type: HUMAN OTC DRUG LABEL
Date: 20250109

ACTIVE INGREDIENTS: SODIUM FLUORIDE 0.37 mg/440 mg
INACTIVE INGREDIENTS: STEVIA LEAF; ERYTHRITOL; XYLITOL; SODIUM BICARBONATE; SODIUM COCOYL ISETHIONATE; XANTHAN GUM; CALCIUM CARBONATE; MAGNESIUM STEARATE; STRAWBERRY

Kaylaan Strawberry Toothpaste Tablet Refill